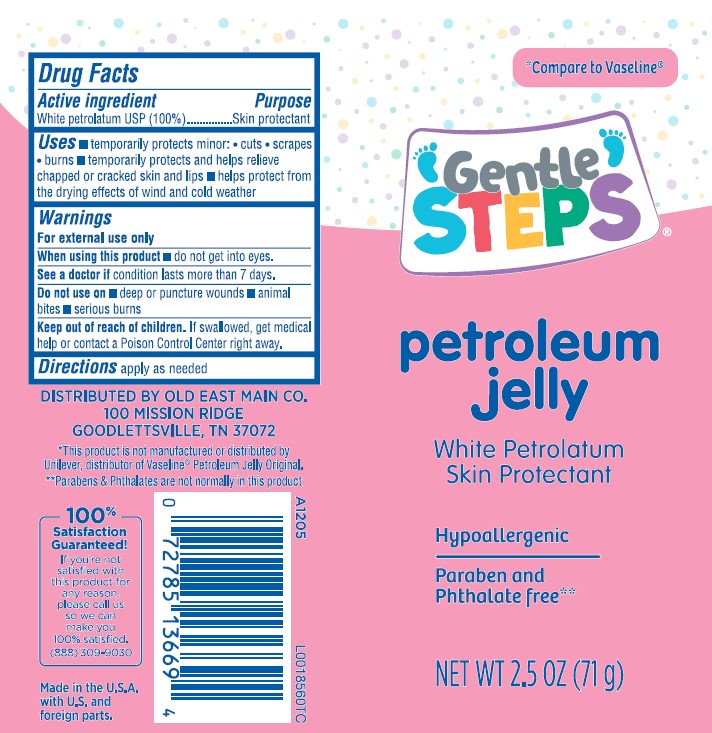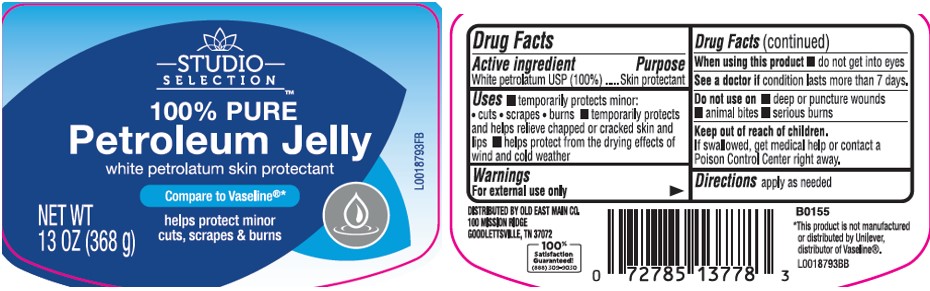 DRUG LABEL: Pure petroleum
NDC: 55910-069 | Form: JELLY
Manufacturer: Old East Main Co.
Category: otc | Type: HUMAN OTC DRUG LABEL
Date: 20260302

ACTIVE INGREDIENTS: PETROLATUM 1 g/1 g

Gentle Steps_Studio Selection 069.001/069AA
Petroleum Jelly

Active ingredients

White Petrolatum USP (100%)

Purpose

Skin protectant

Use

■ temporarily protects minor: ■ cuts ■ scrapes ■ burns
■ temporarily protects and helps relieve chapped or cracked skin and lips
■ helps protect from the drying effects of wind and cold weather

Warnings

For external use only

When using this product

- do not get into eyes

See a doctor if

condition lasts more than 7 days.

Do not use

- deep or puncture wounds
- animal bites
- serious burns

Keep out of reach of children.

If swallowed, get medical help or contact a Poison Control Center right away.

Directions

apply as needed

Inactive Ingredient

None

Dislcaimer

*This product is not manufactured or distributed by Unliever, distributor of Vaseline®.

Adverse Reactions

DISTRIBUTED BY OLD EAST MAIN CO.

100 MISSION RIDGE,

GOODLETTSVILLE, TN 37072

100% QUALITY GUARANTEED (888)309-9030

Principal display panel

Gentle Steps

Compare to Vaseline*

petroleum jelly

White Petrolatum

Skin Protectant

NET WT 2.5 OZ (71 g)

Principal display panel

STUDIO SELECTION

100% Pure

Petroleum Jelly

White Petrolatum Skin Protectant

Compare to Vaseline*

Helps protect minor cuts, scrapes & burns

NET WT 13 OZ (368 g)